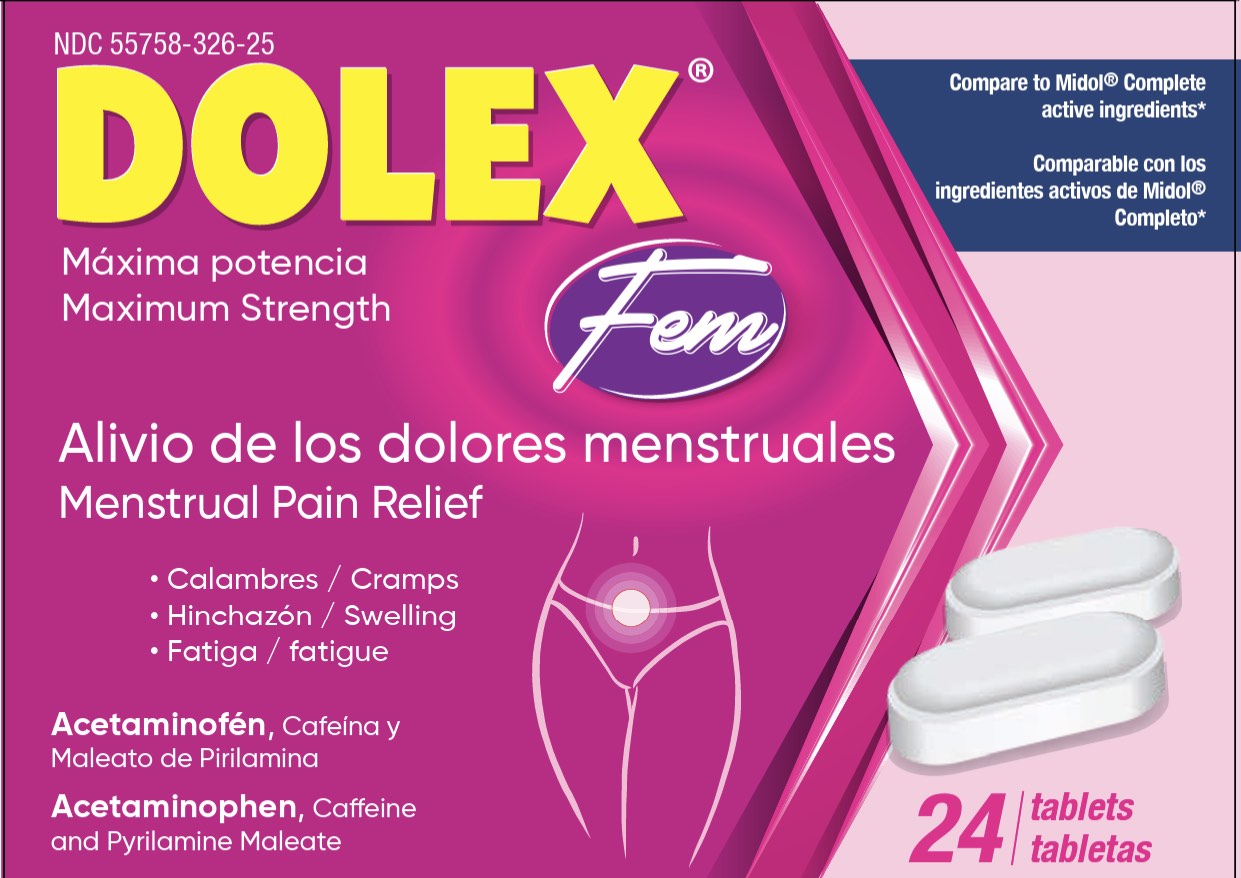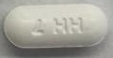 DRUG LABEL: Dolex Fem
NDC: 55758-326 | Form: TABLET, COATED
Manufacturer: Pharmadel LLC
Category: otc | Type: HUMAN OTC DRUG LABEL
Date: 20260205

ACTIVE INGREDIENTS: ACETAMINOPHEN 500 mg/1 1; CAFFEINE 60 mg/1 1; PYRILAMINE MALEATE 15 mg/1 1
INACTIVE INGREDIENTS: STARCH, CORN; SILICON DIOXIDE; TITANIUM DIOXIDE; MICROCRYSTALLINE CELLULOSE; POLYETHYLENE GLYCOL 400; STEARIC ACID; WATER; MAGNESIUM STEARATE; HYPROMELLOSE, UNSPECIFIED; POVIDONE K30; TALC

Dolex Fem (HHH)

Active ingredients & Purposes

.

PURPOSE

Active ingredients (in each tablet) | Purposes
Acetaminophen 500mg............................ | Pain reliever
Caffeing 60mg ......................................... | Diuretic
Pyrilamine maleate 15mg......................... | Anthistamine

Uses

For the temporary relief of these symptoms associated with menstrual periods

- cramps
- bloating
- water- weight gain
- headache
- backache
- Muscle aches
- fatigue

Warnings

Liver warning: This product contains acetaminophen. Severe liver damage may occur if you take:

more than 6 tablets in 24 hours, which is the maximum daily amount for this product
with other drugs containing acetaminophen
3 or more alcoholic drinks every day while using this product.

Allergy alert: Acetaminophen may cause severe skin or severe allergic reactions. Symptoms may include:

- skin reddening
- blisters
- rash
- If a skin or general allergic reaction occurs, stop use and seek medical help right away.

Caffeine warning: The recommended dose of this product contains about as much caffeine as a cup of coffee. Limit the use of caffeine-containing medications, foods, or beverages while taking this product because too much caffeine may cause nervousness, irritability,sleeplessness, and, occasionally, rapid heart beat.

Do not use

- with any other drug containing acetaminophen (prescription or nonprescription). If you are not sure whether a drug contains acetaminophen, ask a doctor or pharmacist.
- if allergic to any of the ingredients in this product

Ask a doctor before use if you have

- liver disease
- glaucoma
- a breathing problem such as emphysema or chronic bronchitis
- difficulty in urination due to enlargement of the prostate gland

Ask a doctor or pharmacist before use if you are

- taking the blood thinning drug warfarin
- taking sedatives or tranquilizers

When using this product

- excitability may occur, especially in children
- alcohol, sedatives, and tranquilizers may increase drowsiness
- avoid alcoholic beverages while taking this product
- use caution when driving a motor vehicle or operating machinery

Stop use and ask a doctor if

- new symptoms occur
- redness or swelling is present
- pain gets worse or lasts more than 7 days
- fever gets worse or lasts more than 3 days

If pregnant or breast-feeding,

ask a health professional before use.

Keep out of reach of children.

In case of an accidental overdose, get medical help or contact a Poison Control Center right away. Prompt medical attention is critical for adults as well as for children even if you do not notice any signs or symptoms.

Directions

- Do not exceed recommended dose
- adultos and children 12 years of age and over: take two (2) caplets, every 6 hours, do not exceed 6 caplets in a 24- hour period
- children under 12 years of age: do not use

Other information

- Store at room temperature 77-86°F (25-30°C)

Inactive ingredients

corn starch, hypromellose, magnesium stearate, microcrystalline cellulose, polyethylene glycol 400, povidone k30, silicon dioxide, stearic acid, talc, titanium dioxide, water

Questions or comments?

1-866-359-3478 (M-F) 9AM - 5PM or www.pharmadel.com

*This product is not manufactured or distributed by Bayer Healthcare LLC owner of the registered trademark MidolⓇ Complete.